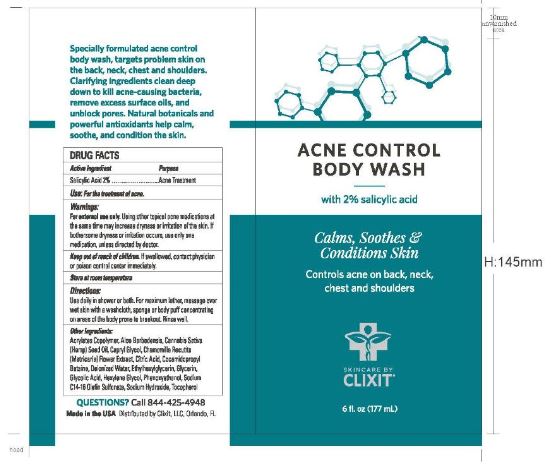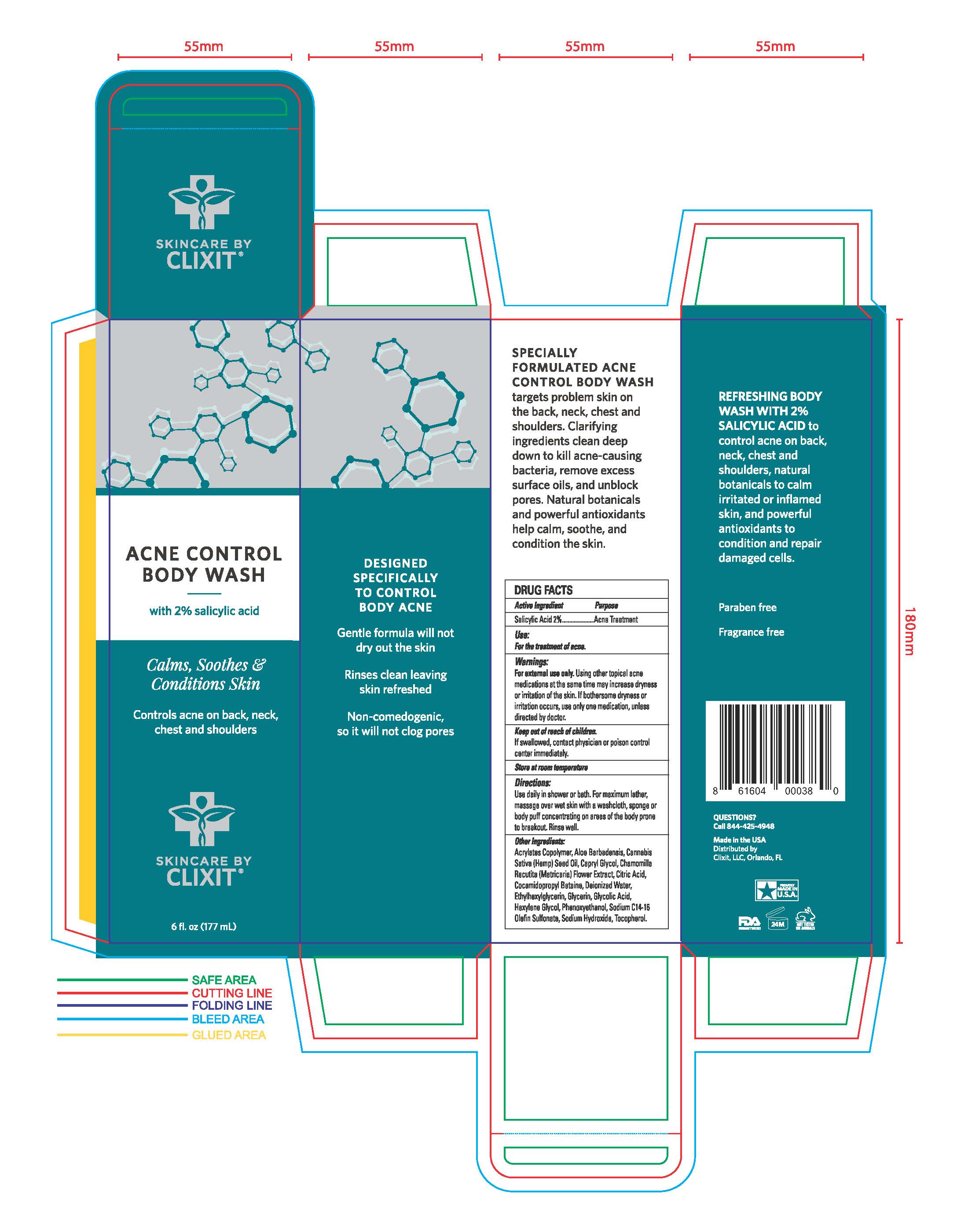 DRUG LABEL: Acne Control Body Wash
NDC: 76348-441 | Form: SOAP
Manufacturer: RENU LABORATORIES INC.
Category: otc | Type: HUMAN OTC DRUG LABEL
Date: 20190913

ACTIVE INGREDIENTS: SALICYLIC ACID 3.4 g/168 g
INACTIVE INGREDIENTS: PHENOXYETHANOL; CAPRYLYL GLYCOL; SODIUM HYDROXIDE; GLYCOLIC ACID; TOCOPHEROL; ALOE; ETHYLHEXYLGLYCERIN; CHAMOMILE; CANNABIS SATIVA SEED OIL; GLYCERIN; WATER; COCAMIDOPROPYL BETAINE; CITRIC ACID ACETATE; ACRYLIC ACID/ISOPHORONE DIISOCYANATE/PEG-27 COPOLYMER; SODIUM C14-16 OLEFIN SULFONATE

CLIXIT ACNE CONTROL BODY WASH

Active Ingredient

Salicylic Acid

Two percent

Keep out of reach of children. If swallowed, contact physician or poison control center immediately.

Purpose

Acne Treatment

QUESTIONS

Call 844 425 4948

Made in the USA

Distributed by Clixit, LLC Orlando, FL

Warnings

For external use only Using other topical acne medications at the same time may increase dryness or irritation of the skin

If bothersome dryness or irritation occurs use only one medication unless directed by doctor

Use:

For the treatment of acne.

Directions

Use daily in shower or bath

For maximum lather massage over wet skin with a washcloth sponge or body puff concentrating on areas of the body prone to breakout

Rinse well

RECENT MAJOR CHANGES

Punctuation marks changed only

9/2019

Other Ingredients:

Acrylates Copolymer, Aloe Barbadensis, Cannabis Sativa (Hemp) Seed Oil, Capryl Glycol, Chamomilla Recutita (Matricaria) Flower Extract, Citric Acid, Cocamidopropyl Betaine, Deionized Water, Ethylhexylglycerin, Glycerin, Glycolic Acid, Hexylene Glycol, Phenoxyethanol, Sodium C14-16 Olefin Sulfonate, Sodium Hydroxide, Tocopherol.